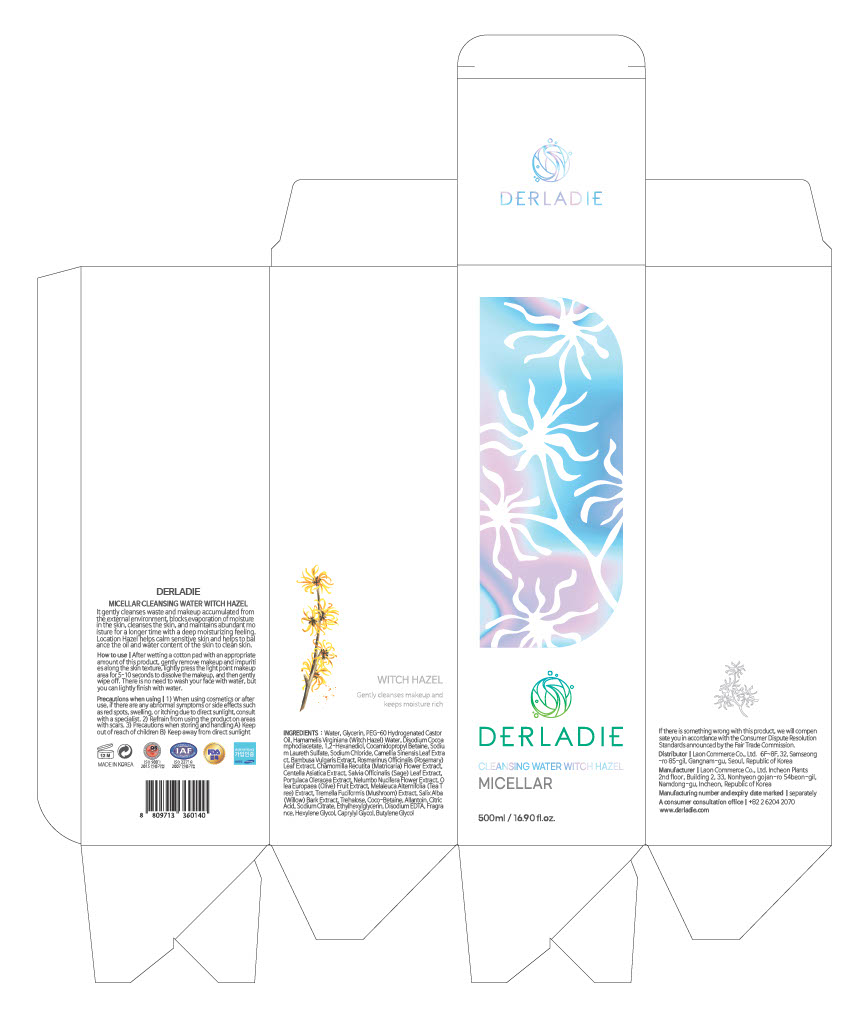 DRUG LABEL: DERLADIE MICELLAR CLEANSING WATER WITCH HAZEL
NDC: 82083-0017 | Form: LIQUID
Manufacturer: LAON COMMERCE co ltd
Category: otc | Type: HUMAN OTC DRUG LABEL
Date: 20230427

ACTIVE INGREDIENTS: WITCH HAZEL 1.984 g/100 mL; ALLANTOIN 0.1 g/100 mL
INACTIVE INGREDIENTS: WATER

ACTIVE INGREDIENT

Hamamelis Virginiana (Witch Hazel) Water, Allantoin

INACTIVE INGREDIENT

Water
Glycerin
PEG-60 Hydrogenated Castor Oil
Disodium Cocoamphodiacetate
1,2-Hexanediol
Cocamidopropyl Betaine
Sodium Laureth Sulfate
Sodium Chloride
Camellia Sinensis Leaf Extract
Bambusa Vulgaris Extract
Rosmarinus Officinalis (Rosemary) Leaf Extract
Chamomilla Recutita (Matricaria) Flower Extract
Centella Asiatica Extract
Salvia Officinalis (Sage) Leaf Extract
Portulaca Oleracea Extract
Nelumbo Nucifera Flower Extract
Olea Europaea (Olive) Fruit Extract
Melaleuca Alternifolia (Tea Tree) Extract
Tremella Fuciformis (Mushroom) Extract
Salix Alba (Willow) Bark Extract
Trehalose
Coco-Betaine
Citric Acid
Sodium Citrate
Ethylhexylglycerin
Disodium EDTA
Fragrance
Hexylene Glycol
Caprylyl Glycol
Butylene Glycol

PURPOSE

skin protect

KEEP OUT OF REACH OF THE CHILDREN

INDICATIONS AND USAGE

After wetting a cotton pad with an appropriate

amount of this product, gently remove makeup and impurities along the skin texture, lightly press the light point makeup area for 5-10 seconds to dissolve the makeup, and then gently wipe off. There is no need to wash your face with water, but

you can lightly finish with water.

WARNINGS

1) When using cosmetics or after

use, if there are any abnormal symptoms or side effects such as red spots, swelling, or itching due to direct sunlight, consult with a specialist. 2) Refrain from using the product on areas with scars. 3) Precautions when storing and handling A) Keep

out of reach of children B) Keep away from direct sunlight

DOSAGE AND ADMINISTRATION

topical use only